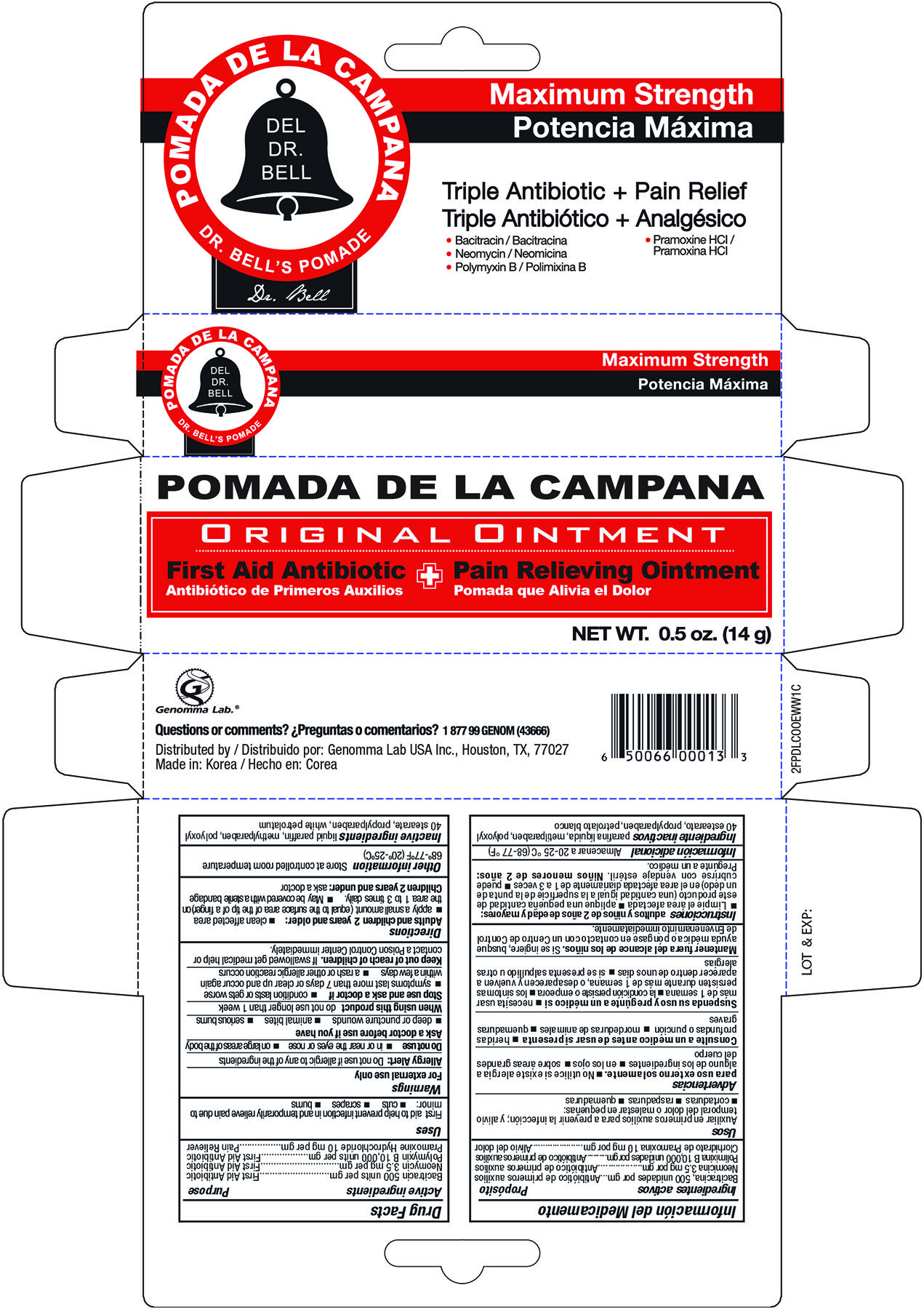 DRUG LABEL: Pomada De La Campana Triple Antibiotic Pain Relief
NDC: 50066-013 | Form: CREAM
Manufacturer: Genomma Lab USA, Inc.
Category: otc | Type: HUMAN OTC DRUG LABEL
Date: 20161027

ACTIVE INGREDIENTS: BACITRACIN 500 [USP'U]/1 g; NEOMYCIN SULFATE 3.5 mg/1 g; POLYMYXIN B SULFATE 10000 [USP'U]/1 g; PRAMOXINE HYDROCHLORIDE 10 mg/1 g
INACTIVE INGREDIENTS: PARAFFIN; METHYLPARABEN; POLYOXYL 40 STEARATE; PROPYLPARABEN; PETROLATUM

Active Ingredients Purpose

Bacitracin 500 units per gm-------------------------------------------------------------------------First Aid Antibiotic

Neomycin 3.5 mg per gm---------------------------------------------------------------------------First Aid Antibiotic

Polymyxin B 10,000 units per gm------------------------------------------------------------------First Aid Antibiotic

Pramoxine Hydrochoride 10mg---------------------------------------------------------------------First Aid Antibiotic

Uses

First aid to help prevent infection in and temporarily relieve pain due to minor:

Cuts, Scrapes, Burns

WARNINGS

For external use only

Allergey Alert: Do not use if allergic to any of the ingredients

Do not use

in or near the eyes or nose

on large areas of the body

Ask a doctor before use if you have

deep or puncture wounds

animal bites

serious burns

do not use longer than 1 week

Stop use and ask a doctor if

condition lasts or gets worse

symptoms last more than 7 days or clear up and occur again within a few days

a rash or other allergic reaction occurs

Keep out of reach of children

If swallowed get medical help or contact a Poison Control Center immediately.

Directions

Adults and children 2 years and older:

clean affected area

apply a small amount (equal to the surface area of the tip of a finger) on the area 1 to 3 times daily.

May be covered with a sterile bandage

Children 2 years and under: ask a doctor

Other information

Store at controlled room temperature at 68°-77° (20°-25°)

Inactive Ingredient

Liquid paraffin, methylparaben, polyoxyl 40 stearate, propylparaben, white petrolatum

DOSAGE AND ADMINISTRATION

Distributed by:

Genomma lab USA Inc.,

Houston, TX, 77027

Made in Korea